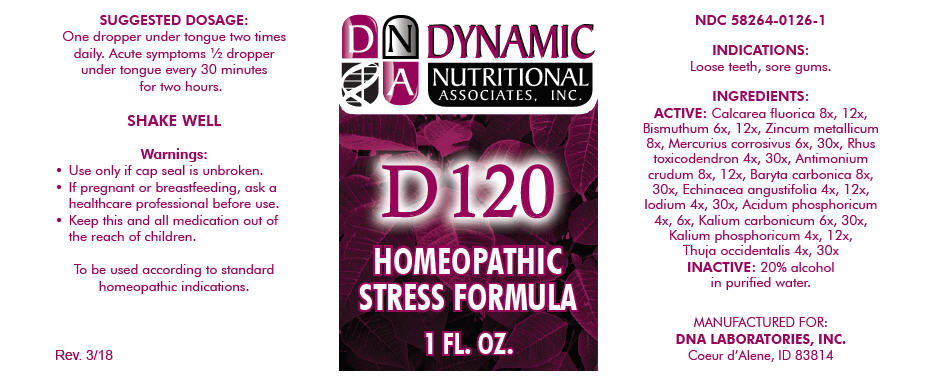 DRUG LABEL: D-120
NDC: 58264-0126 | Form: SOLUTION
Manufacturer: DNA Labs, Inc.
Category: homeopathic | Type: HUMAN OTC DRUG LABEL
Date: 20250113

ACTIVE INGREDIENTS: CALCIUM FLUORIDE 8 [hp_X]/1 mL; BISMUTH SUBNITRATE 6 [hp_X]/1 mL; ZINC 8 [hp_X]/1 mL; MERCURIC CHLORIDE 6 [hp_X]/1 mL; TOXICODENDRON PUBESCENS LEAF 4 [hp_X]/1 mL; ANTIMONY TRISULFIDE 8 [hp_X]/1 mL; BARIUM CARBONATE 8 [hp_X]/1 mL; ECHINACEA ANGUSTIFOLIA 4 [hp_X]/1 mL; IODINE 4 [hp_X]/1 mL; PHOSPHORIC ACID 4 [hp_X]/1 mL; POTASSIUM CARBONATE 6 [hp_X]/1 mL; DIBASIC POTASSIUM PHOSPHATE 4 [hp_X]/1 mL; THUJA OCCIDENTALIS LEAFY TWIG 4 [hp_X]/1 mL
INACTIVE INGREDIENTS: ALCOHOL; WATER

D-120

NDC 58264-0126-1

INDICATIONS

PURPOSE

Loose teeth, sore gums.

INGREDIENTS

ACTIVE

Calcarea fluorica 8x, 12x, Bismuthum 6x, 12x, Zincum metallicum 8x, Mercurius corrosivus 6x, 30x, Rhus toxicodendron 4x, 30x, Antimonium crudum 8x, 12x, Baryta carbonica 8x, 30x, Echinacea angustifolia 4x, 12x, Iodium 4x, 30x, Acidum phosphoricum 4x, 6x, Kalium carbonicum 6x, 30x, Kalium phosphoricum 4x, 12x, Thuja occidentalis 4x, 30x

INACTIVE

20% alcohol in purified water.

SUGGESTED DOSAGE

One dropper under tongue two times daily. Acute symptoms ½ dropper under tongue every 30 minutes for two hours.

STORAGE AND HANDLING

SHAKE WELL

Warnings

- Use only if cap seal is unbroken.

PREGNANCY OR BREAST FEEDING

- If pregnant or breastfeeding, ask a healthcare professional before use.

KEEP OUT OF REACH OF CHILDREN

- Keep this and all medication out of the reach of children.

To be used according to standard homeopathic indications.

PRINCIPAL DISPLAY PANEL - 1 FL. OZ. Bottle Label

DYNAMIC
NUTRITIONAL
ASSOCIATES, INC.

D 120

HOMEOPATHIC
STRESS FORMULA

1 FL. OZ.